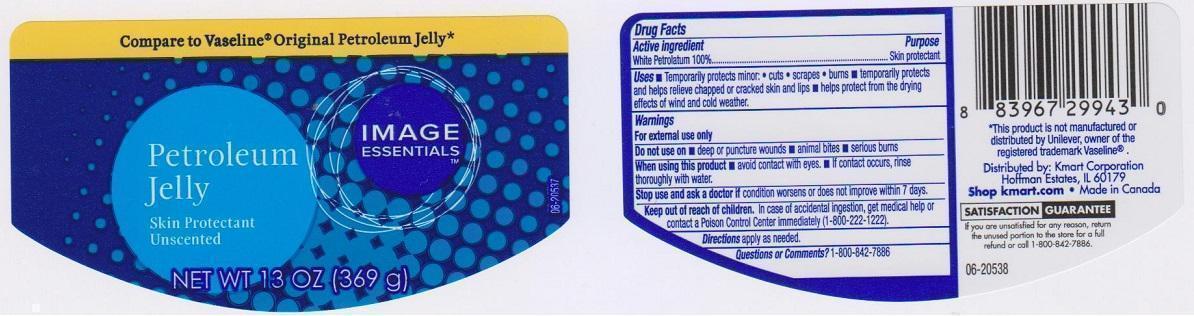 DRUG LABEL: IMAGE ESSENTIALS
NDC: 49738-350 | Form: JELLY
Manufacturer: KMART CORPORATION
Category: otc | Type: HUMAN OTC DRUG LABEL
Date: 20150506

ACTIVE INGREDIENTS: PETROLATUM 1000 mg/1 g
INACTIVE INGREDIENTS: MINERAL OIL

DRUG FACTS

ACTIVE INGREDIENT

WHITE PETROLATUM 100%

PURPOSE

SKIN PROTECTANT

USES

TEMPORARILY PROTECTS MINOR:

- CUTS
- SCRAPES
- BURNS
- TEMPORARILY PROTECTS AND HELPS RELIEVE CHAPPED OR CRACKED SKIN AND LIPS
- HELPS PROTECT FROM THE DRYING EFFECTS OF WIND AND COLD WEATHER

WARNINGS

FOR EXTERNAL USE ONLY

DO NOT USE ON

- DEEP OR PUNCTURE WOUNDS
- ANIMAL BITES
- SERIOUS BURNS

WHEN USING THIS PRODUCT

- AVOID CONTACT WITH EYES
- IF CONTACT OCCURS, RINSE THOROUGHLY WITH WATER

STOP USE AND ASK A DOCTOR IF

CONDITION WORSENS OR DOES NOT IMPROVE WITHIN 7 DAYS

KEEP OUT OF REACH OF CHILDREN

IN CASE OF ACCIDENTAL INGESTION, GET MEDICAL HELP OR CONTACT A POISON CONTROL CENTER IMMEDIATELY (1-800-222-1222)

DIRECTIONS

APPLY AS NEEDED

QUESTIONS OR COMMENTS?

1-800-842-7886

INACTIVE INGREDIENT

MINERAL OIL